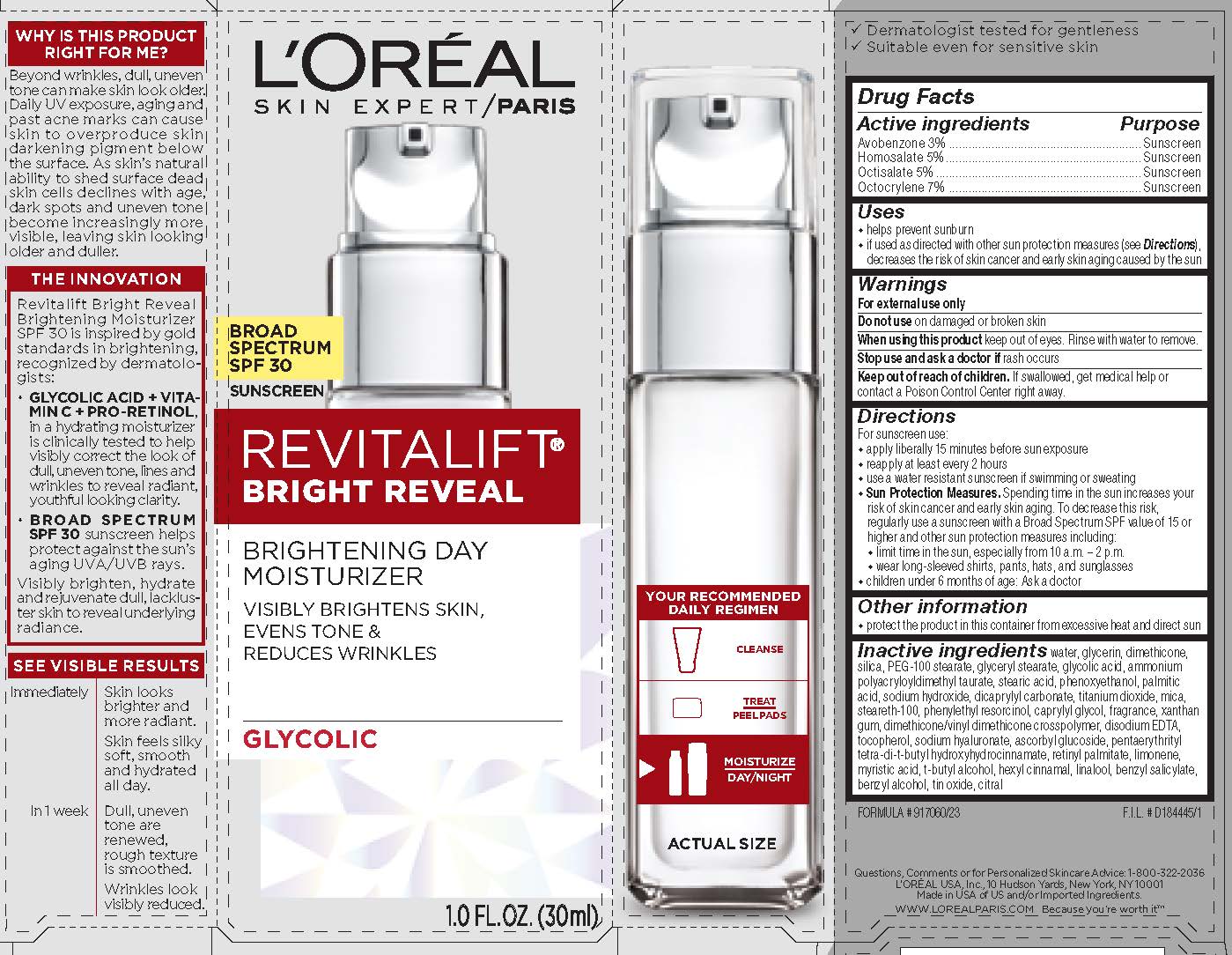 DRUG LABEL: LOreal Paris Skin Expert Revitalift Bright Reveal Brightening Day Moisturizer Broad Spectrum SPF 30 Sunscreen
NDC: 49967-504 | Form: LOTION
Manufacturer: L'Oreal USA Products Inc
Category: otc | Type: HUMAN OTC DRUG LABEL
Date: 20240101

ACTIVE INGREDIENTS: AVOBENZONE 30 mg/1 mL; HOMOSALATE 50 mg/1 mL; OCTISALATE 50 mg/1 mL; OCTOCRYLENE 70 mg/1 mL
INACTIVE INGREDIENTS: WATER; GLYCERIN; DIMETHICONE; SILICON DIOXIDE; PEG-100 STEARATE; GLYCERYL MONOSTEARATE; GLYCOLIC ACID; STEARIC ACID; PHENOXYETHANOL; PALMITIC ACID; SODIUM HYDROXIDE; DICAPRYLYL CARBONATE; TITANIUM DIOXIDE; MICA; STEARETH-100; PHENYLETHYL RESORCINOL; CAPRYLYL GLYCOL; XANTHAN GUM; DIMETHICONE/VINYL DIMETHICONE CROSSPOLYMER (HARD PARTICLE); EDETATE DISODIUM; TOCOPHEROL; HYALURONATE SODIUM; ASCORBYL GLUCOSIDE; PENTAERYTHRITOL TETRAKIS(3-(3,5-DI-TERT-BUTYL-4-HYDROXYPHENYL)PROPIONATE); VITAMIN A PALMITATE; LIMONENE, (+)-; MYRISTIC ACID; TERT-BUTYL ALCOHOL; .ALPHA.-HEXYLCINNAMALDEHYDE; LINALOOL, (+/-)-; BENZYL SALICYLATE; BENZYL ALCOHOL; STANNIC OXIDE; CITRAL

Drug Facts

Active ingredients

Avobenzone 3%

Homosalate 5%

Octisalate 5%

Octocrylene 7%

Purpose

Sunscreen

Uses

- helps prevent sunburn

- if used as directed with other sun protection measures (see Directions), decreases the risk of skin cancer and early skin aging caused by the sun

Warnings

For external use only

Do not use

on damaged or broken skin

When using this product

keep out of eyes. Rinse with water to remove.

Stop use and ask a doctor if

rash occurs

Keep out of reach of children.

If swallowed, get medical help or contact a Poison Control Center right away.

Directions

For sunscreen use:

● apply liberally 15 minutes before sun exposure

● reapply at least every 2 hours

● use a water resistant sunscreen if swimming or sweating

● Sun Protection Measures. Spending time in the sun increases your risk of skin cancer and early skin aging. To decrease this risk, regularly use a sunscreen with a Broad Spectrum SPF value of 15 or higher and other sun protection measures including:

● limit time in the sun, especially from 10 a.m. – 2 p.m.

● wear long-sleeved shirts, pants, hats, and sunglasses

● children under 6 months of age: Ask a doctor

Other information

protect the product in this container from excessive heat and direct sun

Inactive ingredients

water, glycerin, dimethicone, silica, PEG-100 stearate, glyceryl stearate, glycolic acid, ammonium polyacryloyldimethyl taurate, stearic acid, phenoxyethanol, palmitic acid, sodium hydroxide, dicaprylyl carbonate, titanium dioxide, mica, steareth-100, phenylethyl resorcinol, caprylyl glycol, fragrance, xanthan gum, dimethicone/vinyl dimethicone crosspolymer, disodium EDTA, tocopherol, sodium hylauronate, ascorbyl glucoside, pentaerythrityl tetra-di-t-butyl hydroxyhydrocinnamate, retinyl palmitate, limonene, myristic acid, t-butyl alcohol, hexyl cinnamal, linalool, benzyl salicylate, benzyl alcohol, tin oxide, citral